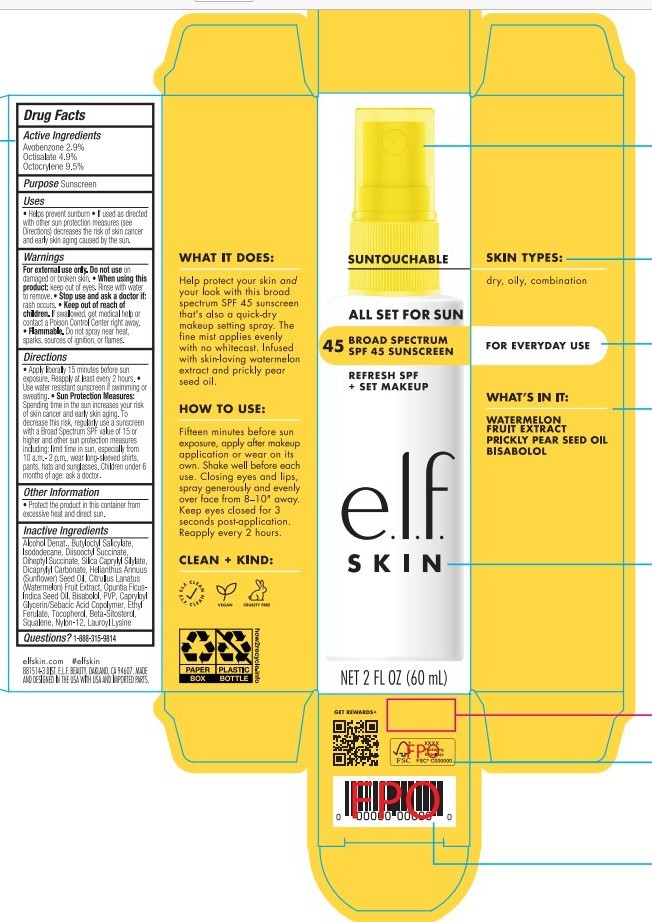 DRUG LABEL: e.l.f. All Set For Sun SPF 45 Sunscreen
NDC: 76354-453 | Form: SPRAY
Manufacturer: e.l.f. Cosmetics, Inc.
Category: otc | Type: HUMAN OTC DRUG LABEL
Date: 20251203

ACTIVE INGREDIENTS: OCTISALATE 49 mg/1 mL; OCTOCRYLENE 95 mg/1 mL; AVOBENZONE 29 mg/1 mL
INACTIVE INGREDIENTS: DICAPRYLYL CARBONATE; BETA-SITOSTEROL; BUTYLOCTYL SALICYLATE; HELIANTHUS ANNUUS (SUNFLOWER) SEED OIL; TOCOPHEROL; CITRULLUS LANATUS (WATERMELON) SEED; NYLON-12; SILICA DIMETHYL SILYLATE; DIHEPTYL SUCCINATE; DIISOOCTYL SEBACATE; OPUNTIA FICUS-INDICA SEED OIL; ISODODECANE; CAPRYLOYL GLYCERIN/SEBACIC ACID COPOLYMER (2000 MPA.S); ALCOHOL; SQUALENE; PVP; LAUROYL LYSINE; ETHYL FERULATE; BISABOLOL

e.l.f. All Set For Sun SPF45

Active Ingredients

Avobenzone 3%

Octisalate 2.9%

Octocrylene 9.5%

Purpose

Sunscreen

Uses

- Helps prevent sunburn
- if used as directed with other sun protection measures (see Directions) decreases the risk of skin cancer and early skin aging caused by the sun.

Warnings

For external use only. Do not use on damaged or broken skin.

- When using this product: keep out of eyes. rinse wiht water to remove.
- Stop use and ask a doctor if: rash occurs.
- Keep out of reach of children. If swallowed, get medical help or contact a Poison Control Center right away.
- Flammable. Do not spray near heat, sparks sources of ignition, or flames.

Do not use on damaged or broken skin.

When using this product: keep out of eyes. Rinse with water to remove.

Ask a doctor if: rash occurs.

Keep out of reach of children. If swallowed, contact poison control center or seek medical help right away.

OTHER SAFETY INFORMATION

Flammable. Do not spray near heat, sparks, sources of ignition, or flames.

Directions

- Apply liberallly 15 minutes before sun exposure. Reapply at least every 2 hours.
- Use water resistant sunscreen if swimming or sweating.
- Sun Protection Measures: Spending time in the sun increases your risk of skin cancer and early skin aging. to decrease this risk, regularly use a sunscreen with a Broad Spectrum SPF value of 15 or higher and other sun protection measures including: limit time in sun, especially from 10 a.m. - 2 p.m., wear long-sleeved shirts, pants, hats and sunglasses. Children under 6 months of age: ask a doctor.

Other Information

- Protect the product in this container from excessive heat and direct sun.

Inactive Ingredients

Alcohol Denat., Octocrylene, Octisalate, Butyloctyl Salicylate, Isododecane, Diisooctyl Succinate, Avobenzone, Diheptyl Succinate, Silica Caprylyl Silylate, Dicaprylyl Carbonate, Helianthus Annuus (Sunflower) Seed Oil, Citrullus Lanatus (Watermelon) Fruit Extract, Opuntia Ficus-Indica Seed Oil, Bisabolol, PVP, Capryloyl Glycerin/Sebacic Acid Copolymer, Ethyl Ferulate, Tocopherol, Beta-Sitosterol, Squalene, Nylon-12, Lauroyl Lysine

Questions?

1-888-315-9814